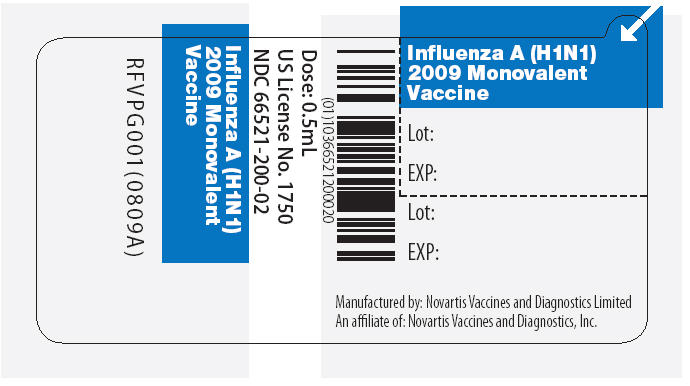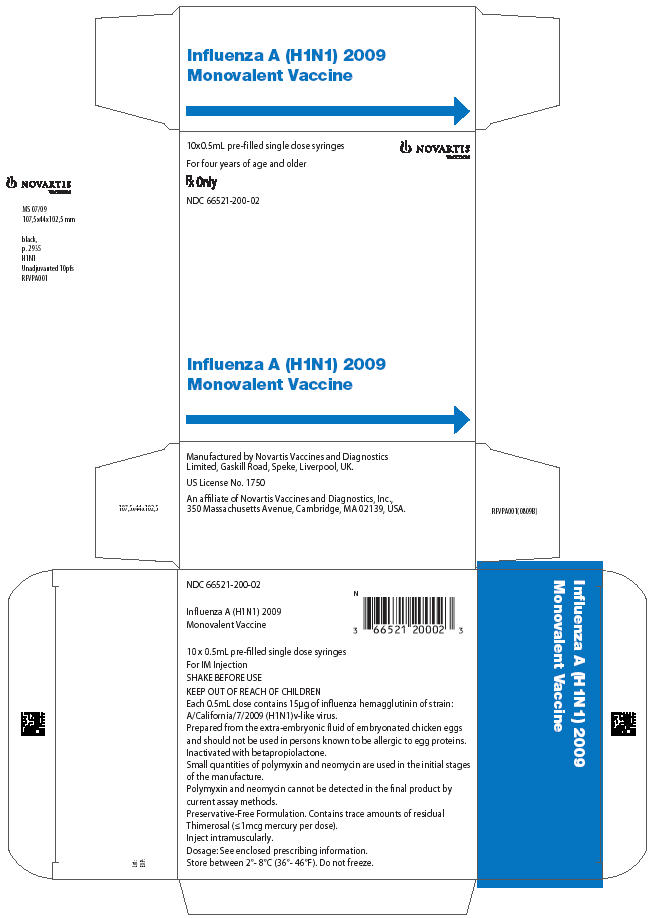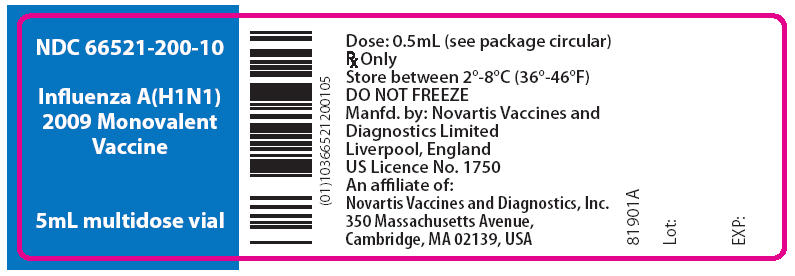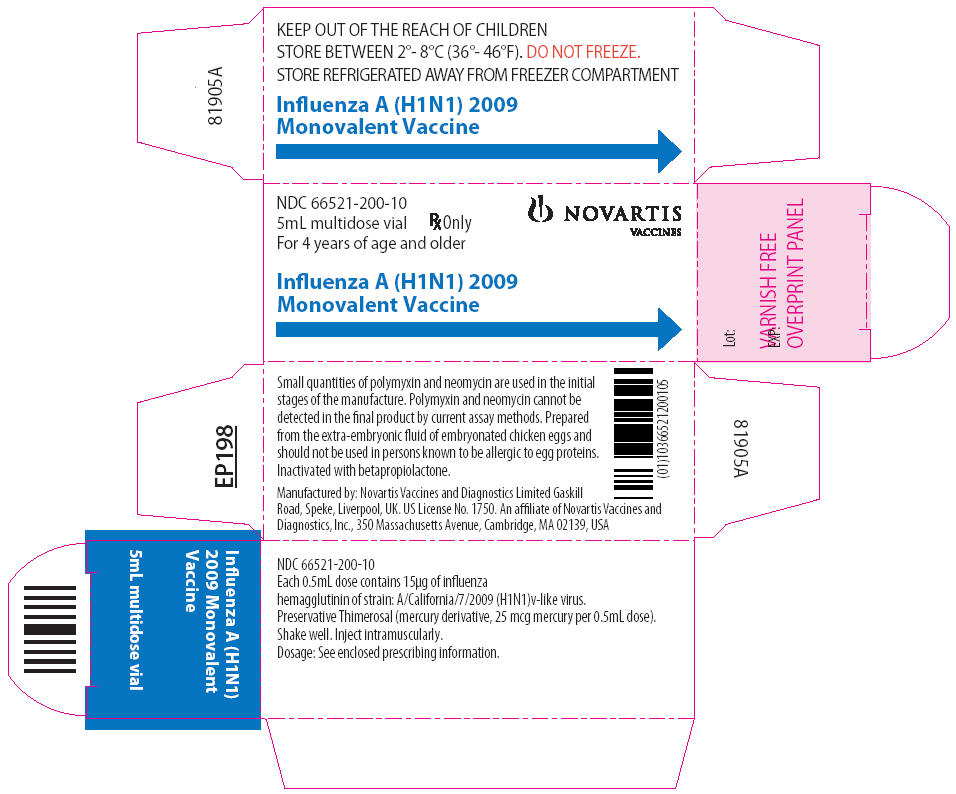 DRUG LABEL: Influenza A (H1N1) 2009 Monovalent Vaccine
NDC: 66521-200 | Form: INJECTION, SUSPENSION
Manufacturer: Novartis Vaccines and Diagnostics Ltd
Category: other | Type: VACCINE LABEL
Date: 20091016

ACTIVE INGREDIENTS: INFLUENZA A VIRUS A/CALIFORNIA/7/2009(H1N1)-LIKE HEMAGGLUTININ ANTIGEN (PROPIOLACTONE INACTIVATED) 15 ug/0.5 mL

HIGHLIGHTS OF PRESCRIBING INFORMATION

These highlights do not include all the information needed to use Influenza A (H1N1) 2009 Monovalent Vaccine safely and effectively. See full prescribing information for Influenza A (H1N1) 2009 Monovalent Vaccine.
Influenza A (H1N1) 2009 Monovalent Vaccine
Manufactured by Novartis Vaccines and Diagnostics Ltd.
Suspension for Intramuscular Injection
Initial U.S. Approval: 2009

1 Indications and Usage

- Influenza A (H1N1) 2009 Monovalent Vaccine is an inactivated influenza virus vaccine indicated for active immunization of persons 4 years of age and older against influenza disease caused by pandemic (H1N1) 2009 virus (1).

2 Dosage and Administration

Based on currently available information the vaccination regimen is as follows:

- Children 4 through 9 years of age: Two 0.5-mL intramuscular injections approximately 1 month apart (2.2)
- Children 10 through 17 years of age: A single 0.5-mL intramuscular injection (2.2)
- Adults 18 years of age and older: A single 0.5-mL intramuscular injection (2.2)

3 DOSAGE FORMS AND STRENGTHS

Influenza A (H1N1) 2009 Monovalent Vaccine, a sterile suspension for intramuscular injection, is supplied in two presentations:

- Prefilled single dose syringe, 0.5-mL. Thimerosal, a mercury derivative used during manufacture, is removed by subsequent purification steps to a trace amount (≤ 1 mcg mercury per 0.5-mL dose) (3, 11)
- Multidose vial, 5-mL. Contains thimerosal, a mercury derivative (25 mcg mercury per 0.5-mL dose). Thimerosal is added as preservative. (3,11)

4 CONTRAINDICATIONS

- History of systemic hypersensitivity reactions to egg proteins, or any other component of Influenza A (H1N1) 2009 Monovalent Vaccine, or life-threatening reactions to previous influenza vaccinations. (4, 11)

5 WARNINGS AND PRECAUTIONS

- If Guillain-Barré syndrome has occurred within 6 weeks of receipt of prior influenza vaccine, the decision to give Influenza A (H1N1) 2009 Monovalent Vaccine should be based on careful consideration of the potential benefits and risks. (5.1)
- Immunocompromised persons may have a reduced immune response to Influenza A (H1N1) 2009 Monovalent Vaccine. (5.2)

6 ADVERSE REACTIONS

Adverse Reaction information is based on studies conducted with seasonal trivalent Influenza Virus Vaccine manufactured by Novartis (FLUVIRIN).

The most frequently reported adverse reactions are mild hypersensitivity reactions (such as rash), local reactions at the injection site, and influenza-like symptoms. (6)

To report SUSPECTED ADVERSE REACTIONS contact Novartis Vaccines at 1-800-244-7668, or VAERS at 1-800-822-7967 and www.vaers.hhs.gov.

7 DRUG INTERACTIONS

- Do not mix with any other vaccine in the same syringe or vial. (7.1)
- Immunosuppressive therapies may reduce immune response to Influenza A (H1N1) 2009 Monovalent Vaccine. (7.2)

8 USE IN SPECIFIC POPULATIONS

- Safety and effectiveness of Influenza A (H1N1) 2009 Monovalent Vaccine have not been established in pregnant women, nursing mothers or children less than 4 years of age. (8.1, 8.3, 8.4)
- Antibody responses to the trivalent seasonal Influenza Virus Vaccine manufactured by Novartis (FLUVIRIN) were lower in the geriatric population than in younger subjects. (8.5)

FULL PRESCRIBING INFORMATION

1 Indications and Usage

Influenza A (H1N1) 2009 Monovalent Vaccine is an inactivated influenza virus vaccine indicated for immunization of persons 4 years of age and older against influenza disease caused by pandemic (H1N1) 2009 virus.

2 Dosage and Administration

2.1 Preparation for Administration

Inspect Influenza A (H1N1) 2009 Monovalent Vaccine syringes and multidose vials visually for particulate matter and/or discoloration prior to administration. If either of these conditions exists, the vaccine should not be administered.

Shake the syringe vigorously before administering the vaccine and shake the multidose vial preparation each time before withdrawing a dose of vaccine.

Between uses, return the multidose vial to the recommended storage conditions between 2º and 8ºC (36º and 46ºF). Do not freeze. Discard if the vaccine has been frozen.

A separate syringe and needle or a sterile disposable unit should be used for each injection to prevent transmission of infectious agents from one person to another. Needles should be disposed of properly and not recapped.

It is recommended that small syringes (0.5-mL or 1-mL) should be used to minimize any product loss.

2.2 Recommended Dose and Schedule

Clinical studies are ongoing with Influenza A (H1N1) 2009 Monovalent Vaccine to determine the optimal dosage, number of doses and schedule.

Available data show that children 9 years of age and younger are largely serologically naïve to the pandemic (H1N1) 2009 virus (15.1). Based upon these data Influenza A (H1N1) 2009 Monovalent Vaccine should be administered as follows:

Children (4 to 17 years of age):

Children 4 through 9 years of age should receive two 0.5mL doses by intramuscular injection approximately 1 month apart.

Children 10 through 17 years of age should receive a single 0.5-mL intramuscular injection.

The needle size may range from 7/8 to 1¼ inches, depending on the size of the child’s deltoid muscle, and should be of sufficient length to penetrate the muscle tissue. The anterolateral thigh can be used, but the needle should be longer, usually 1 inch.

The vaccine should not be injected in the gluteal region or areas where there may be a major nerve trunk.

Adults (18 years of age and older):

Influenza A (H1N1) 2009 Monovalent Vaccine should be administered as a single 0.5-mL intramuscular injection preferably in the region of the deltoid muscle of the upper arm.

A needle of ≥1 inch is preferred because needles <1 inch might be of insufficient length to penetrate muscle tissue in certain adults.

The vaccine should not be injected in the gluteal region or areas where there may be a major nerve trunk.

3 DOSAGE FORMS AND STRENGTHS

Influenza A (H1N1) 2009 Monovalent Vaccine is a sterile suspension for intramuscular injection. [see DESCRIPTION (11) for the complete list of ingredients]

Influenza A (H1N1) 2009 Monovalent Vaccine is available in two presentations:

1) Prefilled single dose syringe, 0.5-mL. Thimerosal, a mercury derivative used during manufacture, is removed by subsequent purification steps to a trace amount (≤ 1 mcg mercury per 0.5-mL dose).

2) Multidose vial, 5-mL. Contains thimerosal, a mercury derivative, added as a preservative. Each 0.5-mL dose from the multidose vial contains 25 mcg mercury.

4 CONTRAINDICATIONS

4.1 Hypersensitivity

Influenza A (H1N1) 2009 Monovalent Vaccine should not be administered to anyone with known systemic hypersensitivity reactions to egg proteins (eggs or egg products), or to any component of Influenza A (H1N1) 2009 Monovalent Vaccine, or who has had a life-threatening reaction to previous influenza vaccinations [see DESCRIPTION (11)].

5 WARNINGS AND PRECAUTIONS

5.1 Guillain-Barré Syndrome

If Guillain-Barré syndrome has occurred within 6 weeks of receipt of prior influenza vaccine, the decision to give Influenza A (H1N1) 2009 Monovalent Vaccine should be based on careful consideration of the potential benefits and risks.

5.2 Altered Immunocompetence

If Influenza A (H1N1) 2009 Monovalent Vaccine is administered to immunocompromised persons, including individuals receiving immunosuppressive therapy, the expected immune response may not be obtained.

5.3 Preventing and Managing Allergic Reactions

Prior to administration of any dose of Influenza A (H1N1) 2009 Monovalent Vaccine, the healthcare provider should review the patient’s prior immunization history for possible adverse events, to determine the existence of any contraindication to immunization with Influenza A (H1N1) 2009 Monovalent Vaccine and to allow an assessment of benefits and risks. Appropriate medical treatment and supervision must be available to manage possible anaphylactic reactions following administration of the vaccine.

5.4 Limitations of Vaccine Effectiveness

Vaccination with Influenza A (H1N1) 2009 Monovalent Vaccine may not protect all individuals.

6 ADVERSE REACTIONS

Novartis’ Influenza A (H1N1) 2009 Monovalent Vaccine and seasonal trivalent Influenza Virus Vaccine (FLUVIRIN®) are manufactured by the same process. The data in this section were obtained from clinical studies and postmarketing experience with FLUVIRIN.

6.1 Overall Adverse Reaction Profile

Serious allergic reactions, including anaphylactic shock, have been observed in individuals receiving FLUVIRIN during postmarketing surveillance.

6.2 Clinical Trial Experience

Adverse event information from clinical trials provides a basis for identifying adverse events that appear to be related to vaccine use and for approximating the rates of these events. However, because clinical trials are conducted under widely varying conditions, the adverse reaction rates observed in the clinical trials of a vaccine cannot be directly compared to rates in the clinical trials of another vaccine, and may not reflect rates observed in clinical practice.

Adult and Geriatric Subjects

Safety data were collected in a total of 2768 adult and geriatric subjects (18 years of age and older) who have received FLUVIRIN in 29 clinical studies since 1982.

In 9 clinical studies since 1997, among 1261 recipients of FLUVIRIN, 745 (59%) were women; 1211 (96%) were White, 23 (2%) Asian, 15 (1%) Black and 12 (1%) other; 370 (29%) of subjects were elderly (≥65 years of age). All studies have been conducted in the UK, apart from a study run in the US in 2005-2006 where FLUVIRIN was used as a comparator for an unlicensed vaccine.

After vaccination, the subjects were observed for 30 minutes for hypersensitivity or other immediate reactions. Subjects were instructed to complete a diary card for three days following immunization (i.e. Day 1 to 4) to collect local and systemic reactions (see Tables 1 and 2). All local and systemic adverse events were considered to be at least possibly related to the vaccine. Local and systemic reactions mostly began between day 1 and day 2. The overall adverse events reported in clinical trials since 1998 in at least 5% of the subjects are summarized in Table 3.

TABLE 1 Solicited Adverse Events in the First 72-96 Hours after Administration of FLUVIRIN in Adult (18-64 years of age) and Geriatric (≥65 years of age) Subjects.
 | 1998-1999*§ |  | 1999-2000*§ |  | 2000-2001*§
 | 18-64 yrs | ≥ 65 yrs | 18-64 yrs | ≥ 65 yrs | 18-64 yrs | ≥ 65 yrs
 | N = 66 | N = 44 | N = 76 | N = 34 | N = 75 | N = 35
Local Adverse Events
Pain | 16 (24%) | 4 (9%) | 16 (21%) | - | 9 (12%) | -
Mass | 7 (11%) | 1 (2%) | 4 (5%) | - | 8 (11%) | 1 (3%)
Inflammation | 5 (8%) | 2 (5%) | 6 (8%) | - | 7 (9%) | 1 (3%)
Ecchymosis | 4 (6%) | 1 (2%) | 3 (4%) | 1 (3%) | 4 (5%) | -
Edema | 2 (3%) | 1 (2%) | 1 (1%) | 2 (6%) | 3 (4%) | 1 (3%)
Reaction | 2 (3%) | - | 2 (3%) | - | 4 (5%) | 1 (3%)
Hemorrhage | - | - | 1 (1%) | - | - | -
Systemic Adverse Events
Headache | 7 (11%) | 1 (2%) | 17 (22%) | 3 (9%) | 4 (5%) | -
Fatigue | 3 (5%) | 2 (5%) | 4 (5%) | 1 (3%) | 3 (4%) | -
Malaise | 2 (3%) | 1 (2%) | 2 (3%) | 1 (3%) | 1 (1%) | -
Myalgia | 1 (2%) | - | 2 (3%) | - | - | -
Fever | 1 (2%) | - | 1 (1%) | - | - | -
Arthralgia | - | 1 (2%) | - | 1 (3%) | - | -
Sweating | - | - | 3 (4%) | - | 1 (1%) | 1 (3%)
 | 2001-2002*^ |  | 2002-2003*^ |  | 2004-2005*^
 | 18-64 yrs | ≥ 65 yrs | 18-64 yrs | ≥ 65 yrs | 18-64 yrs | ≥ 65 yrs
 | N = 75 | N = 35 | N = 107 | N = 88 | N = 74 | N = 61
Local Adverse Events
Pain | 12 (16%) | 1 (3%) | 14 (13%) | 7 (8%) | 15 (20%) | 9 (15%)
Mass | 4 (5%) | 1 (3%) | - | - | - | -
Ecchymosis | 2 (3%) | - | 3 (3%) | 3 (3%) | 2 (3%) | 1 (2%)
Edema | 2 (3%) | 1 (3%) | 6 (6%) | 2 (2%) | - | -
Erythema | 5 (7%) | - | 11 (10%) | 5 (6%) | 16 (22%) | 5 (8%)
Swelling | - | - | - | - | 11 (15%) | 4 (7%)
Reaction | - | - | 2 (2%) | - | - | -
Induration | - | - | 14 (13%) | 3 (3%) | 11 (15%) | 1 (2%)
Pruritus | - | - | 1 (1%) | - | - | -
Systemic Adverse Events
Headache | 8 (11%) | 1 (3%) | 12 (11%) | 9 (10%) | 14 (19%) | 3 (5%)
Fatigue | 1 (1%) | 1 (3%) | - | - | 5 (7%) | 2 (3%)
Malaise | 3 (4%) | - | 3 (3%) | 4 (5%) | 1 (1%) | 1 (2%)
Myalgia | 3 (4%) | - | 5 (5%) | 3 (3%) | 8 (11%) | 1 (2%)
Fever | - | - | - | 1 (1%) | - | -
Arthralgia | - | - | 2 (2%) | - | 1 (1%) | -
Sweating | 3 (4%) | 1 (3%) | - | 2 (2%) | - | -
Shivering | - | - | - | 1 (1%) | - | -
Results reported to the nearest whole percent; Fever defined as >38°C
– not reported
* Solicited adverse events in the first 72 hours after administration of FLUVIRIN
§ Solicited adverse events reported by COSTART preferred term
^ Solicited adverse events reported by MEDDRA preferred term

TABLE 2 Solicited Adverse Events in the First 72 Hours after Administration of FLUVIRIN in Adult Subjects (18-49 years of age).
 | 2005-2006 US Trial
 | FLUVIRIN
 | N = 304
Local Adverse Events
Pain | 168 (55%)
Erythema | 48 (16%)
Ecchymosis | 22 (7%)
Induration | 19 (6%)
Swelling | 16 (5%)
Systemic Adverse Events
Headache | 91 (30%)
Myalgia | 64 (21%)
Malaise | 58 (19%)
Fatigue | 56 (18%)
Sore throat | 23 (8%)
Chills | 22 (7%)
Nausea | 21 (7%)
Arthralgia | 20 (7%)
Sweating | 17 (6%)
Cough | 18 (6%)
Wheezing | 4 (1%)
Chest tightness | 4 (1%)
Other difficulties breathing | 3 (1%)
Facial edema | -
Results reported to the nearest whole percent
– not reported

TABLE 3 Adverse Events Reported by at least 5% of Subjects in Clinical Trials since 1998
 | 1998-1999§ |  |  | 1999-2000§ |  |  | 2000-2001§
 | 18-64 yrs | ≥ 65 yrs |  | 18-64 yrs | ≥ 65 yrs |  | 18-64 yrs | ≥ 65 yrs
 | N = 66 | N = 44 |  | N = 76 | N = 34 |  | N = 75 | N = 35
Adverse Events
Fatigue | 8 (12%) | 2 (5%) |  | 8 (11%) | 2 (6%) |  | 5 (7%) | -
Back pain | 4 (6%) | 3 (7%) |  | - | - |  | - | -
Cough increased | 2 (3%) | 2 (5%) |  | - | - |  | - | -
Ecchymosis | 4 (6%) | 1 (2%) |  | 4 (5%) | 1 (3%) |  | 5 (7%) | -
Fever | 3 (5%) | - |  | - | - |  | - | -
Headache | 12 (18%) | 5 (11%) |  | 22 (29%) | 5 (15%) |  | 14 (19%) | 2 (6%)
Infection | 3 (5%) | 2 (5%) |  | - | - |  | - | -
Malaise | 4 (6%) | 4 (9%) |  | 4 (5%) | 1 (3%) |  | - | -
Migraine | 4 (6%) | 1 (2%) |  | - | - |  | - | -
Myalgia | 4 (6%) | 1 (2%) |  | - | - |  | - | -
Sweating | 5 (8%) | 1 (2%) |  | - | - |  | - | -
Rhinitis | 3 (5%) | 1 (2%) |  | - | - |  | 5 (7%) | 2 (6%)
Pharingitis | 6 (9%) | 1 (2%) |  | 10 (13%) | - |  | 6 (8%) | -
Arthralgia | - | - |  | - | 2 (6%) |  | - | -
Injection site pain | 16 (24%) | 4 (9%) |  | 16 (21%) | - |  | 9 (12%) | -
Injection site ecchymosis | 4 (6%) | 1 (2%) |  | - | - |  | 4 (5%) | -
Injection site mass | 7 (11%) | 1 (2%) |  | 4 (5%) | - |  | 8 (11%) | 1 (3%)
Injection site edema | - | - |  | 1 (1%) | 2 (6%) |  | - | -
Injection site inflammation | 5 (8%) | 2 (5%) |  | 6 (8%) | - |  | 7 (9%) | 1 (3%)
Injection site reaction | - | - |  | - | - |  | 4 (5%) | 1 (3%)
 | 2001-2002^ |  |  | 2002-2003^ |  |  | 2004-2005^
 | 18-64 yrs |  | ≥ 65 yrs | 18-64 yrs |  | ≥ 65 yrs | 18-64 yrs | ≥ 65 yrs
 | N = 75 |  | N = 35 | N = 107 |  | N = 88 | N = 74 | N = 61
Adverse Events
Fatigue | 5 (7%) |  | 4 (11%) | 11 (10%) |  | 8 (9%) | 4 (5%) | 2 (3%)
Hypertension | - |  | - | 1 (1%) |  | 4 (5%) | - | -
Rinorrhea | - |  | - | 2 (2%) |  | 5 (6%) | - | -
Headache | 20 (27%) |  | 2 (6%) | 35 (33%) |  | 18 (20%) | 12 (16%) | 1 (2%)
Malaise | 6 (8%) |  | 1 (3%) | 13 (12%) |  | 8 (9%) | - | -
Myalgia | 4 (5%) |  | 1 (3%) | 10 (9%) |  | 4 (5%) | - | -
Sweating | 3 (4%) |  | 3 (9%) | 2 (2%) |  | 5 (6%) | - | -
Rhinitis | 4 (5%) |  | - | - |  | - | - | -
Pharingitis | - |  | - | - |  | - | 6 (8%) | -
Arthralgia | - |  | - | 5 (5%) |  | 4 (5%) | - | -
Sore throat | 4 (5%) |  | 1 (3%) | 5 (5%) |  | 4 (5%) | - | -
Injection site pain | 13 (17%) |  | 3 (9%) | 14 (13%) |  | 7 (8%) | 6 (8%) | 2 (3%)
Injection site ecchymosis | 4 (5%) |  | 1 (3%) | 4 (4%) |  | 4 (5%) | - | -
Injection site erythema | 5 (7%) |  | 2 (6%) | 11 (10%) |  | 5 (6%) | 4 (5%) | -
Injection site mass | 4 (5%) |  | 1 (3%) | - |  | - | - | -
Injection site edema | - |  | - | 6 (6%) |  | 2 (2%) | 4 (5%) | 1 (2%)
Injection site induration | - |  | - | 14 (13%) |  | 3 (3%) | 7 (9%) | -
Results reported to the nearest whole percent; Fever defined as >38°C
– not reaching the cut-off of 5%
§ Solicited adverse events reported by COSTART preferred term
^ Solicited adverse events reported by MEDDRA preferred term

Adults (18 to 64 years of age)

In adult subjects, solicited local adverse events occurred with similar frequency in all trials. The most common solicited adverse events occurring in the first 96 hours after administration (Tables 1 and 2) were associated with the injection site (such as pain, erythema, mass, induration and swelling) but were generally mild/moderate and transient. The most common solicited systemic adverse events were headache and myalgia.

The most common overall events in adult subjects (18-64 years of age) were headache, fatigue, injection site reactions (pain, mass, erythema, and induration) and malaise (Table 3).

Geriatric Subjects (65 years of age and older)

In geriatric subjects, solicited local and systemic adverse events occurred less frequently than in adult subjects. The most common solicited local and systemic adverse events were injection site pain, and headache (Tables 1 and 2). All were considered mild/moderate and were transient.

The most common overall events in elderly subjects (≥65 years of age) were headache and fatigue.

Only 11 serious adverse events in adult and geriatric subjects (18 years and older) have been reported to date from all the trials performed. These serious adverse events were a minor stroke experienced by a 67 year old subject 14 days after vaccination (1990), death of an 82 year old subject 35 days after vaccination (1990) in very early studies; death of a 72 year old subject 19 days after vaccination (1998-1999), a hospitalization for hemorrhoidectomy of a 38 year old male subject (1999-2000), a severe respiratory tract infection experienced by a 74 year old subject 12 days after vaccination (2002-2003), a planned transurethral resection of the prostate in a subject with prior history of prostatism (2004-2005), two cases of influenza (2005-2006), a drug overdose (2005-2006), cholelithiasis (2005-2006) and a nasal septal operation (2005-2006). None of these events were considered causally related to vaccination.

Clinical Trial Experience in Pediatric Subjects

In 1987 a clinical study was carried out in 38 ‘at risk’ children aged between 4 and 12 years (17 females and 21 males). To record the safety of FLUVIRIN, participants recorded their symptoms on a diary card during the three days after vaccination and noted any further symptoms they thought were attributable to the vaccine. The only reactions recorded were tenderness at the site of vaccination in 21% of the participants on day 1, which was still present in 16% on day 2 and 5% on day 3. In one child, the tenderness was also accompanied by redness at the site of injection for two days. The reactions were not age-dependent and there was no bias towards the younger children.

Three clinical studies were carried out between 1995 and 2004 in a total of 520 pediatric subjects (age range 6 - 47 months). Of these, 285 healthy subjects plus 41 ‘at risk’ subjects received FLUVIRIN. No serious adverse events were reported.

FLUVIRIN and Influenza A (H1N1) 2009 Monovalent Vaccine should only be used for the immunization of persons aged 4 years and over.

6.3 Postmarketing Experience

The following additional adverse reactions have been reported during post-approval use of FLUVIRIN. Because these reactions are reported voluntarily from a population of uncertain size, it is not always possible to reliably estimate their frequency or establish a causal relationship to vaccine exposure. Adverse events described here are included because: a) they represent reactions which are known to occur following immunizations generally or influenza immunizations specifically; b) they are potentially serious; or c) the frequency of reporting.

- Body as a whole: Local injection site reactions (including pain, pain limiting limb movement, redness, swelling, warmth, ecchymosis, induration), hot flashes/flushes; chills; fever; malaise; shivering; fatigue; asthenia; facial edema.
- Immune system disorders: Hypersensitivity reactions (including throat and/or mouth edema). In rare cases, hypersensitivity reactions have lead to anaphylactic shock and death.
- Cardiovascular disorders: Vasculitis (in rare cases with transient renal involvement), syncope shortly after vaccination.
- Digestive disorders: Diarrhea; nausea; vomiting; abdominal pain.
- Blood and lymphatic disorders: Local lymphadenopathy; transient thrombocytopenia.
- Metabolic and nutritional disorders: Loss of appetite.
- Musculoskeletal: Arthralgia; myalgia; myasthenia.
- Nervous system disorders: Headache; dizziness; neuralgia; paraesthesia; confusion; febrile convulsions; Guillain-Barré Syndrome; myelitis (including encephalomyelitis and transverse myelitis); neuropathy (including neuritis); paralysis (including Bell’s Palsy).
- Respiratory disorders: Dyspnea; chest pain; cough; pharyngitis; rhinitis.
- Skin and appendages: Stevens-Johnson syndrome; sweating; pruritus; urticaria; rash (including non-specific, maculopapular, and vesiculobulbous).

6.4 Other Adverse Reactions Associated with Influenza Vaccination

Anaphylaxis has been reported after administration of FLUVIRIN. Although FLUVIRIN and Influenza A (H1N1) 2009 Monovalent Vaccine contain only a limited quantity of egg protein, this protein can induce immediate hypersensitivity reactions among persons who have severe egg allergy. Allergic reactions include hives, angioedema, allergic asthma, and systemic anaphylaxis [see CONTRAINDICATIONS (4)].

The 1976 swine influenza vaccine was associated with an increased frequency of Guillain-Barré syndrome (GBS). Evidence for a causal relation of GBS with subsequent vaccines prepared from other influenza viruses is unclear. If influenza vaccine does pose a risk, it is probably slightly more than 1 additional case/1 million persons vaccinated.

Neurological disorders temporally associated with influenza vaccination such as encephalopathy, optic neuritis/neuropathy, partial facial paralysis, and brachial plexus neuropathy have been reported.

Microscopic polyangiitis (vasculitis) has been reported temporally associated with influenza vaccination.

7 DRUG INTERACTIONS

7.1 Concomitant Administration with Other Vaccines

There are no data to assess the concomitant administration of Influenza A (H1N1) 2009 Monovalent Vaccine with other vaccines. If Influenza A (H1N1) 2009 Monovalent Vaccine is to be given at the same time as another injectable vaccine(s), the vaccines should always be administered at different injection sites.

Influenza A (H1N1) 2009 Monovalent Vaccine should not be mixed with any other vaccine in the same syringe or vial.

7.2 Concurrent Use with Immunosuppressive Therapies

Immunosuppressive therapies, including irradiation, antimetabolites, alkylating agents, cytotoxic drugs, and corticosteroids (used in greater than physiologic doses), may reduce the immune response to Influenza A (H1N1) 2009 Monovalent Vaccine.

8 USE IN SPECIFIC POPULATIONS

Novartis’ Influenza A (H1N1) 2009 Monovalent Vaccine and seasonal trivalent Influenza Virus Vaccine (FLUVIRIN) are manufactured by the same process. Available information for FLUVIRIN is provided in this section.

8.1 Pregnancy

Pregnancy Category C: Animal reproduction studies have not been conducted with Influenza A (H1N1) 2009 Monovalent Vaccine or FLUVIRIN. It is also not known whether Influenza A (H1N1) 2009 Monovalent Vaccine or FLUVIRIN can cause fetal harm when administered to a pregnant woman or can affect reproduction capacity. Influenza A (H1N1) 2009 Monovalent Vaccine should be given to a pregnant woman only if clearly needed.

8.3 Nursing Mothers

It is not known whether FLUVIRIN or Influenza A (H1N1) 2009 Monovalent Vaccine is excreted in human milk. Because many drugs are excreted in human milk, caution should be exercised when Influenza A (H1N1) 2009 Monovalent Vaccine is administered to a nursing woman.

8.4 Pediatric Use

Safety and effectiveness in pediatric subjects below the age of 4 years have not been established. [see ADVERSE REACTIONS (6) and CLINICAL STUDIES (14)]

8.5 Geriatric Use

Since 1997, of the total number of geriatric subjects (n = 397) in clinical studies of FLUVIRIN, 29% of adult subjects were 65 years and over, while 2.1% were 75 years and over.

Antibody responses were lower in the geriatric population than in younger subjects. Adverse events occurred less frequently in geriatric subjects (≥65 years) than in younger adults. Other reported clinical experience has not identified differences in responses between the elderly and younger patients. [See ADVERSE REACTION (6) and CLINICAL STUDIES (14)].

11 DESCRIPTION

Influenza A (H1N1) 2009 Monovalent Vaccine is a sub-unit (purified surface antigen) influenza virus vaccine prepared from virus propagated in the allantoic cavity of embryonated hens’ eggs inoculated with a specific type of influenza virus suspension containing neomycin and polymyxin. The influenza virus strain is harvested and clarified by centrifugation and filtration prior to inactivation with betapropiolactone. The inactivated virus is concentrated and purified by zonal centrifugation. The surface antigens, hemagglutinin and neuraminidase, are obtained from the influenza virus particle by further centrifugation in the presence of nonylphenol ethoxylate, a process which removes most of the internal proteins. The nonylphenol ethoxylate is removed from the surface antigen preparation.

Influenza A (H1N1) 2009 Monovalent Vaccine is a homogenized, sterile, slightly opalescent suspension in a phosphate buffered saline. Influenza A (H1N1) 2009 Monovalent Vaccine is formulated to contain 15 mcg hemagglutinin (HA) per 0.5-mL dose of the following virus strain: A/California/7/2009 (H1N1)v-like virus.

The 0.5-mL prefilled syringe presentation is formulated without preservative. Thimerosal, a mercury derivative used during manufacturing, is removed by subsequent purification steps to a trace amount (≤ 1 mcg mercury per 0.5-mL dose).

The 5-mL multidose vial formulation contains thimerosal, a mercury derivative, added as a preservative. Each 0.5-mL dose from the multidose vial contains 25 mcg mercury.

Each dose from the multidose vial or from the prefilled syringe may also contain residual amounts of egg proteins (≤ 1 mcg ovalbumin), polymyxin (≤ 3.75 mcg), neomycin (≤ 2.5 mcg), betapropiolactone (not more than 0.5 mcg) and nonylphenol ethoxylate (not more than 0.015% w/v).

The multidose vial stopper and the syringe stopper/plunger do not contain latex.

12 CLINICAL PHARMACOLOGY

12.1 Mechanism of Action

Influenza illness and its complications follow infection with influenza viruses. Global surveillance of influenza identifies yearly antigenic variants. For example, since 1977, antigenic variants of influenza A (H1N1 and H3N2) viruses and influenza B viruses have been in global circulation. Specific levels of hemagglutination inhibition (HI) antibody titers post-vaccination with inactivated influenza virus vaccine have not been correlated with protection from influenza illness. In some human studies, antibody titer of ≥1:40 have been associated with protection from influenza illness in up to 50% of subjects [see REFERENCES (15.2, 15.3)].

Antibody against one influenza virus type or subtype confers limited or no protection against another. Furthermore, antibody to one antigenic variant of influenza virus might not protect against a new antigenic variant of the same type or subtype.

13 NONCLINICAL TOXICOLOGY

13.1 Carcinogenesis, Mutagenesis, Impairment of Fertility

Neither FLUVIRIN nor the Influenza A (H1N1) 2009 Monovalent Vaccine have been evaluated for carcinogenic or mutagenic potential, or for impairment of fertility.

14 CLINICAL STUDIES

Novartis’ Influenza A (H1N1) 2009 Monovalent Vaccine and seasonal trivalent Influenza Virus Vaccine (FLUVIRIN) are manufactured by the same process. Data in this section were obtained in clinical studies conducted with FLUVIRIN.

Between 1982 and 1991, twelve clinical studies were conducted in healthy adult and geriatric subjects and one in children between 4 and 12 years of age who were considered to be ‘at risk’. Since 1991 an annual clinical study has been conducted in the UK in healthy adults aged 18 years or older. FLUVIRIN was also used as a control in a US clinical trial in adults (18-49 years of age). In all the trials, blood samples were taken prior to vaccination and approximately three weeks after vaccination to assess the immunogenic response to vaccination by measurement of anti-HA antibodies.

Three clinical studies were carried out between 1995 and 2004 in a total of 520 pediatric subjects (age range 6-48 months). Of these, 285 healthy subjects plus 41 ‘at risk’ pediatric subjects, received FLUVIRIN.

Influenza A (H1N1) 2009 Monovalent Vaccine should only be used for the immunization of persons aged 4 years and over.

14.1 Immunogenicity in Adults (18 to 64 years of age)

Tables 4 and 5 show the immunogenicity data for the adult age group. The seven clinical studies presented enrolled a total of 774 adult subjects. In the adult group, for all antigens (A/H1N1, A/H3N2 and B) at least one of the following point estimate criteria was met: the proportion of subjects with seroconversion (post-vaccination titer ≥1:40 from a pre-vaccination titer <1:10) or significant increase (at least a four-fold increase from pre-vaccination titer ≥1:10) in antibody titer was greater than 40%; the geometric mean titer (GMT) increase was >2.5; the proportion of subjects with a post-vaccination hemagglutination inhibition (HI) antibody titer ≥1:40 was greater than 70%.

TABLE 4 Summary of the Seroconversion and Proportion of Subjects Achieving an HI titer ≥1:40 for Adult Subjects
Year/Strain | No. of subjects | Seroconversion ∞ |  |  | HI titer ≥1:40¥
Year/Strain | No. of subjects | N | % | 95% CIΦ | N | % | 95% CIΦ
1998-1999
A/H1N1 |  | 48 | 73 | (62, 83) | 50 | 76 | (65, 86)
A/H3N2 | 66 | 43 | 65 | (54, 77) | 47 | 71 | (60, 82)
B |  | 42 | 64 | (52, 75) | 62 | 94 | (88, 100)
1999-2000
A/H1N1 |  | 45 | 59 | (48, 70) | 50 | 66 | (55, 76)
A/H3N2 | 76 | 51 | 67 | (57, 78) | 66 | 87 | (79, 94)
B |  | 53 | 70 | (59, 80) | 75 | 99 | (96, 100)
2000-2001
A/H1N1 |  | 41 | 55 | (44, 67) | 41 | 55 | (44, 67)
A/H3N2 | 74 | 45 | 61 | (50, 72) | 52 | 84 | (75, 92)
B |  | 50 | 68 | (57, 78) | 73 | 99 | (96, 100)
2001-2002
A/H1N1 |  | 44 | 59 | (48, 70) | 48 | 64 | (53, 75)
A/H3N2 | 75 | 46 | 61 | (50, 72) | 68 | 91 | (84, 97)
B |  | 42 | 56 | (45, 67) | 66 | 88 | (81, 95)
2002-2003
A/H1N1 |  | 62 | 58 | (49, 68) | 73 | 69 | (60, 78)
A/H3N2 | 106 | 72 | 68 | (59, 77) | 93 | 88 | (81, 94)
B |  | 78 | 74 | (65, 82) | 101 | 95 | (91, 99)
2004-2005
A/H1N1 |  | 52 | 70 | (59, 80) | 66 | 89 | (80, 95)
A/H3N2 | 74 | 60 | 81 | (70, 89) | 73 | 99 | (93, 100)
B |  | 57 | 77 | (66, 86) | 69 | 93 | (85, 98)
2005-2006
A/H1N1 |  | 191 | 63 | (57, 68) | 296 | 98 | (95, 99)
A/H3N2 | 303 | 273 | 90 | (86, 93) | 294 | 97 | (94, 99)
B |  | 213 | 70 | (65, 75) | 263 | 87 | (82, 90)
∞ Seroconversion: proportion of subjects with either a post-vaccination HI titer ≥1:40 from a pre-vaccination titer <1:10 or at least a four-fold increase from pre-vaccination HI titer ≥1:10 in antibody titer.
¥ HI titer ≥1:40: proportion of subjects with a post-vaccination titer ≥ 1:40.
Φ 95% CI: 95% confidence interval

TABLE 5 Summary of the Geometric Mean Hemagglutination Inhibition Antibody Titers, Pre- and Post-Immunization, for Adult Subjects
Year/Strain | No. of subjects | Geometric Mean Titer (GMT)
Year/Strain | No. of subjects | Pre-vaccination | Post-vaccination | Fold Increase | (95% CI)*
1998-1999
A/H1N1 |  | 7.26 | 160.87 | 22.16 | (14.25, 34.46)
A/H3N2 | 66 | 8.23 | 87.02 | 10.57 | (6.91, 16.16)
B |  | 20.97 | 231.07 | 110.2 | (6.90, 17.59)
1999-2000
A/H1N1 |  | 7.43 | 58.95 | 7.93 | (5.73, 10.97)
A/H3N2 | 76 | 15.29 | 122.83 | 8.03 | (5.80, 11.13)
B |  | 25.70 | 254.76 | 9.91 | (6.97, 14.10)
2000-2001
A/H1N1 |  | 5.42 | 33.80 | 6.24 | (4.49, 8.69)
A/H3N2 | 74 | 15.98 | 126.01 | 7.89 | (5.61, 11.09)
B |  | 26.24 | 308.25 | 11.75 | (7.73, 17.85)
2001-2002
A/H1N1 |  | 7.76 | 54.78 | 7.06 | (5.24, 9.52)
A/H3N2 | 75 | 23.67 | 153.81 | 6.50 | (4.78, 8.84)
B |  | 19.91 | 107.53 | 5.40 | (3.95, 7.38)
2002-2003
A/H1N1 |  | 7.78 | 60.39 | 7.77 | (5.81, 10.39)
A/H3N2 | 106 | 23.32 | 292.03 | 12.52 | (8.77, 17.87)
B |  | 30.20 | 314.11 | 10.40 | (7.54, 14.34)
2004-2005
A/H1N1 |  | 13 | 159 | 12 | (8.39, 17)
A/H3N2 | 74 | 37 | 658 | 18 | (12, 26)
B |  | 15 | 156 | 11 | (7.87, 14)
2005-2006
A/H1N1 |  | 29 | 232 | 8 | (6.68, 9.59)
A/H3N2 | 303 | 14 | 221 | 15 | (14, 17)
B |  | 13 | 83 | 6.5 | (5.73, 7.37)
* 95% CI: 95% confidence interval

14.2 Immunogenicity in Geriatric Subjects (65 years of age and older)

Tables 6 and 7 show the immunogenicity of FLUVIRIN in the geriatric age group. The six clinical studies presented enrolled a total of 296 geriatric subjects. For each of the influenza antigens, the percentage of subjects who achieved seroconversion and the percentage of subjects who achieved HI titers of ≥1:40 are shown, as well as the fold increase in GMT.

For all antigens (A/H1N1, A/H3N2 and B) at least one of the following point estimate criteria was met: the proportion of subjects with seroconversion (post-vaccination titer ≥1:40 from a pre-vaccination titer <1:10) or significant increase (at least a four-fold increase from pre-vaccination titer ≥1:10) in antibody titer was greater than 30%; the geometric mean titer (GMT) increase was >2.0; the proportion of subjects with a post-vaccination hemagglutination inhibition (HI) antibody titer ≥1:40 was greater than 60%. The pre-specified efficacy criteria were met in each study, although a relatively lower immunogenicity of A/H1N1 strain was seen in the last four studies (the same strain was in each of the formulations).

TABLE 6 Summary of the Seroconversion and Proportion of Subjects Achieving an HI titer ≥1:40 for Geriatric Subjects
Year/Strain | No. of subjects | Seroconversion ∞ |  |  | HI titer ≥1:40¥
Year/Strain | No. of subjects | N | % | 95% CIΦ | N | % | 95% CIΦ
1998-1999
A/H1N1 |  | 33 | 79 | (66, 91) | 38 | 90 | (82, 99)
A/H3N2 | 42 | 33 | 79 | (66, 91) | 36 | 86 | (75, 96)
B |  | 13 | 31 | (17, 45) | 42 | 100 | (100, 100)
1999-2000
A/H1N1 |  | 10 | 29 | (14, 45) | 23 | 68 | (52, 83)
A/H3N2 | 34 | 18 | 53 | (36, 70) | 31 | 91 | (82, 100)
B |  | 9 | 26 | (12, 41) | 32 | 94 | (86, 100)
2000-2001
A/H1N1 |  | 5 | 14 | (3, 26) | 10 | 29 | (14, 44)
A/H3N2 | 35 | 22 | 63 | (47, 79) | 31 | 89 | (78, 99)
B |  | 13 | 37 | (21, 53) | 33 | 94 | (87, 100)
2001-2002
A/H1N1 |  | 5 | 14 | (3, 26) | 14 | 40 | (24, 56)
A/H3N2 | 35 | 15 | 43 | (26, 59) | 33 | 94 | (87, 100)
B |  | 6 | 17 | (5, 30) | 32 | 91 | (82, 100)
2002-2003
A/H1N1 |  | 24 | 27 | (18, 36) | 52 | 58 | (48, 69)
A/H3N2 | 89 | 42 | 47 | (37, 58) | 85 | 96 | (91, 100)
B |  | 41 | 46 | (36, 56) | 86 | 97 | (93, 100)
2004-2005
A/H1N1 |  | 17 | 28 | (17, 41) | 46 | 75 | (63, 86)
A/H3N2 | 61 | 29 | 48 | (35, 61) | 60 | 98 | (91, 100)
B |  | 38 | 62 | (49, 74) | 51 | 84 | (72, 92)
∞ Seroconversion: proportion of subjects with either a post-vaccination HI titer ≥1:40 from a pre-vaccination titer <1:10 or at least a four-fold increase from pre-vaccination HI titer ≥1:10 in antibody titer
¥ HI titer ≥1:40: proportion of subjects with a post-vaccination titer ≥1:40
Φ 95% CI: 95% confidence interval

TABLE 7 Summary of the Geometric Mean Hemagglutination Inhibition Antibody Titers, Pre- and Post-Immunization, for Geriatric Subjects
Year/Strain | No. of subjects | Geometric Mean Titer (GMT)
Year/Strain | No. of subjects | Pre-vaccination | Post-vaccination | Fold Increase | (95% CI)*
1998-1999
A/H1N1 |  | 13.92 | 176.65 | 12.69 | (8.24, 19.56)
A/H3N2 | 42 | 10.69 | 124.92 | 11.69 | (7.02, 19.46)
B |  | 114.1 | 273.56 | 2.40 | (1.82, 3.17)
1999-2000
A/H1N1 |  | 15.82 | 50.58 | 3.20 | (2.13, 4.80)
A/H3N2 | 34 | 28.00 | 133.19 | 4.76 | (2.92, 7.76)
B |  | 57.16 | 127.86 | 2.24 | (1.56, 3.20)
2000-2001
A/H1N1 |  | 6.66 | 18.85 | 2.83 | (1.91, 4.18)
A/H3N2 | 35 | 25.87 | 140.68 | 5.44 | (3.72, 7.96)
B |  | 61.24 | 191.23 | 3.12 | (2.13, 4.59)
2001-2002
A/H1N1 |  | 12.69 | 26.65 | 2.10 | (1.55, 2.84)
A/H3N2 | 35 | 47.33 | 114.26 | 2.41 | (1.73, 3.38)
B |  | 45.49 | 91.89 | 2.02 | (1.47, 2.78)
2002-2003
A/H1N1 |  | 13.29 | 31.92 | 2.40 | (1.90, 3.03)
A/H3N2 | 89 | 65.86 | 272.79 | 4.14 | (3.09, 5.55)
B |  | 74.87 | 288.57 | 3.85 | (2.89, 5.13)
2004-2005
A/H1N1 |  | 21 | 64 | 3.13 | (2.33, 4.2)
A/H3N2 | 61 | 72 | 320 | 4.43 | (3.13, 6.27)
B |  | 20 | 114 | 5.69 | (4.39, 7.38)
* 95% CI: 95% confidence interval

14.3 Immunogenicity in Pediatric Subjects

A small-scale study was conducted in 1987 to evaluate safety and immunogenicity of FLUVIRIN in 38 ‘at risk’ children, with diabetes and/or asthma, or lymphoid leukemia. Thirty-eight participants aged between 4 and 12 years of age were assessed. Ten subjects had diabetes, 21 had asthma, two had both diabetes and asthma, and one had lymphoid leukemia. There were four healthy control subjects. All participants received a single 0.5-mL dose of FLUVIRIN.

Immunogenicity results were obtained for 19 of the 38 subjects enrolled in the study. The point estimate of the percentage of subjects achieving a titer of ≥ 1:40 was 84% for the A/H1N1 strain 79% for the B strain, and 53% for the A/H3N2 strain. The GMT fold increases were 5.8 for the A/H1N1 strain, 40 for the B strain and 17.7 for the A/H3N2 strain.

Three clinical studies were carried out between 1995 and 2004 in a total of 520 pediatric subjects (age range 6-47 months). Of these, 285 healthy subjects plus 41 ‘at risk’ pediatric subjects, received FLUVIRIN.

In a 1995/1996 clinical study, 41 subjects (aged 6-36 months) at increased risk for influenza-related complications received two 0.25-mL doses of FLUVIRIN. At least 49% of subjects showed a ≥4-fold increase in HI antibody titer to all three strains. HI antibody titers of 1:40 or greater were seen in at least 71% of the subjects for all three influenza strains, with increases in geometric mean titer of 6.0-fold or greater to all three strains.

Two clinical studies (1999-2000 and 2004) indicated a lower immunogenicity profile for FLUVIRIN compared with two commercial split vaccines; in a study in the age group 6-48 months the comparator was a US licensed vaccine, Fluzone®, and in another study in the age group 6-36 months the comparator was a non-US licensed inactivated influenza vaccine. Despite the small sample size (a total of 285 healthy subjects received FLUVIRIN in these two clinical studies) the lower immunogenicity profile of FLUVIRIN was greatest versus the comparator vaccines in children <36months but was also evident in those 36-48 months of age, though the differences were less.

Influenza A (H1N1) 2009 Monovalent Vaccine should only be used for the immunization of persons aged 4 years and older.

15 REFERENCES

15.1 CDC. Serum cross-reactive antibody response to a novel influenza A (H1N1) virus after vaccination with seasonal influenza vaccine. MMWR 2009; 58(19): 521-4.

15.2 Hannoun C, Megas F, Piercy J. Immunogenicity and protective efficacy of influenza vaccination. Virus Res 2004; 103:133-138.

15.3 Hobson D, Curry RL, Beare A, et. al. The role of serum hemagglutinin-inhibiting antibody in protection against challenge infection with influenza A2 and B viruses. J Hyg Camb 1972; 767-777.

16 HOW SUPPLIED/STORAGE AND HANDLING

16.1 How Supplied

Influenza A (H1N1) 2009 Monovalent Vaccine is supplied as a 0.5-mL prefilled single dose syringe, package of 10 syringes per carton. NDC 66521-200-02

Influenza A (H1N1) 2009 Monovalent Vaccine is supplied as a 5-mL multidose vial, individually packaged in a carton. NDC 66521-200-10

16.2 Storage and Handling

Store Influenza A (H1N1) 2009 Monovalent Vaccine refrigerated between 2º and 8ºC (36º and 46ºF).

Do not freeze. Discard if the vaccine has been frozen.

Store in the original package to protect from light.

Do not use after the expiration date.

Between uses, return the multidose vial to the recommended storage conditions.

17 PATIENT COUNSELING INFORMATION

Vaccine recipients and guardians should be informed by their health care provider of the potential benefits and risks of immunization with Influenza A (H1N1) 2009 Monovalent Vaccine. When educating vaccine recipients and guardians regarding the potential side effects, clinicians should emphasize that Influenza A (H1N1) 2009 Monovalent Vaccine contains non-infectious particles and cannot cause influenza. Vaccine recipients and guardians should be instructed to report any severe or unusual adverse reactions to their healthcare provider.

Vaccine recipients should be advised that there are two influenza vaccine formulations for this influenza season, the monovalent pandemic (H1N1) 2009 influenza vaccine and seasonal trivalent influenza vaccine.

Manufactured by: Novartis Vaccines and Diagnostics Limited, Speke, Liverpool, UK

An affiliate of: Novartis Vaccines and Diagnostics, Inc., 350 Massachusetts Avenue, Cambridge, MA 02139 USA

1-800-244-7668

PACKAGE LABEL

Package Label - Principal Display Panel - 0.5 mL Pre-Filled Syringe

Package Label - Principal Display Panel - 10 Count Carton

PACKAGE LABEL

Package Label - Principal Display Panel - 5 mL Multi-Dose Vial

Package Label - Principal Display Panel - 1 Count Carton